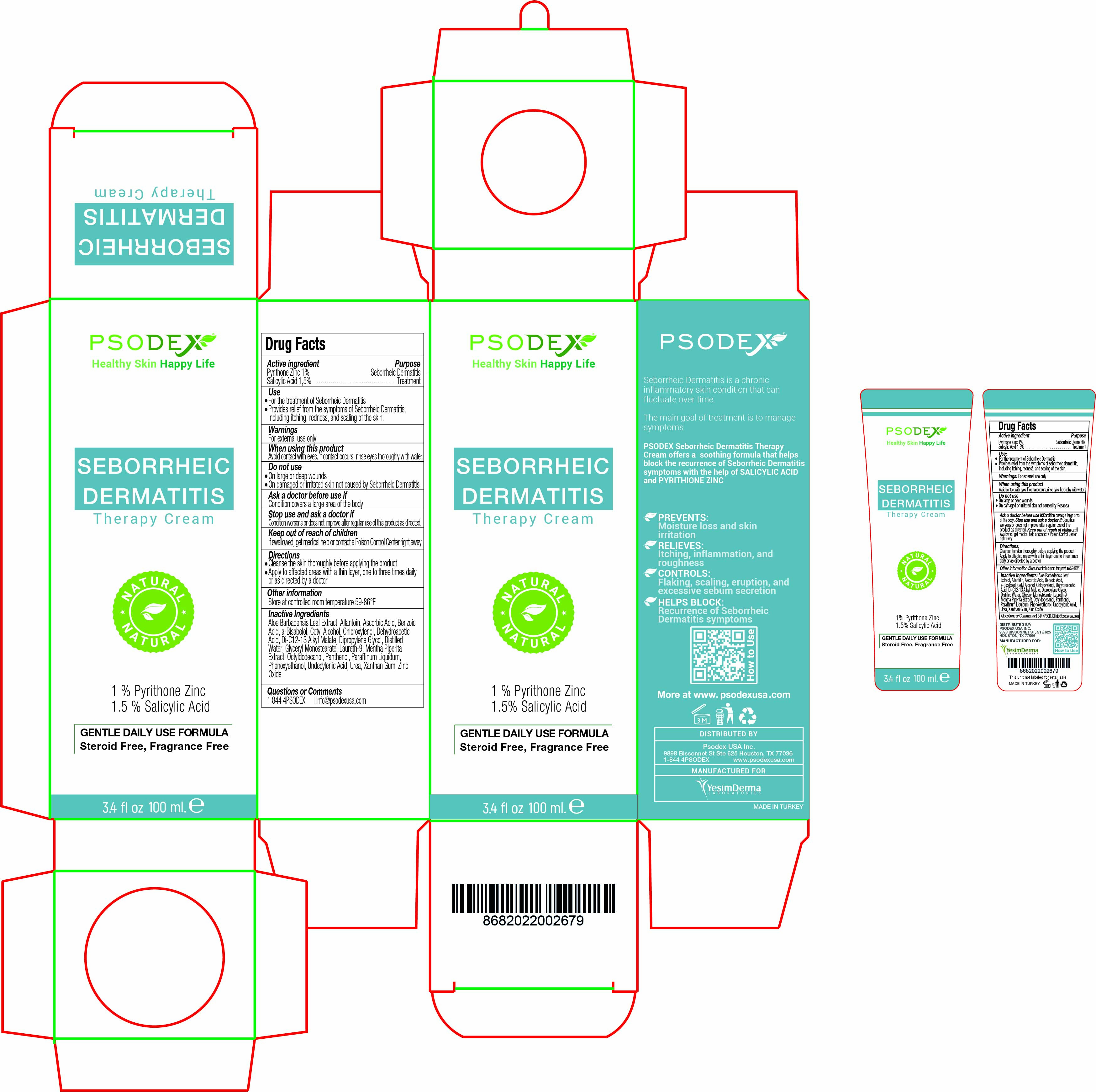 DRUG LABEL: Seborrheic Dermatitis
NDC: 73503-010 | Form: CREAM
Manufacturer: PSODEX USA INC
Category: otc | Type: HUMAN OTC DRUG LABEL
Date: 20231221

ACTIVE INGREDIENTS: PYRITHIONE ZINC 1 g/100 mL; SALICYLIC ACID 1.5 g/100 mL
INACTIVE INGREDIENTS: DIPROPYLENE GLYCOL 0.2 g/100 mL; UNDECYLENIC ACID 2 g/100 mL; ZINC OXIDE 9 g/100 mL; ALLANTOIN 2 g/100 mL; MENTHA PIPERITA LEAF 5 g/100 mL; XANTHAN GUM 0.3 g/100 mL; CETYL ALCOHOL 5 g/100 mL; DI-C12-13 ALKYL MALATE 2 g/100 mL; OCTYLDODECANOL 2 g/100 mL; ASCORBIC ACID 0.5 g/100 mL; ALOE VERA LEAF 5 g/100 mL; PANTHENOL 1 g/100 mL; MINERAL OIL 5 g/100 mL; PHENOXYETHANOL 0.5 g/100 mL; UREA 5 g/100 mL; LEVOMENOL 2 g/100 mL; GLYCERYL MONOSTEARATE 2 g/100 mL; CHLOROXYLENOL 0.5 g/100 mL; BENZOIC ACID 0.25 g/100 mL; DEHYDROACETIC ACID 0.25 g/100 mL; WATER 45 mL/100 mL; POLIDOCANOL 3 g/100 mL

Seborrheic Dermatitis Therapy Cream

Inactive Ingredients

Aloe Barbadensis Leaf Extract, Allantoin, Ascorbic Acid, Benzoic
Acid, a-Bisabolol, Cetyl Alcohol, Chloroxylenol, Dehydroacetic
Acid, Di-C12-13 Alkyl Malate, Dipropylene Glycol, Distilled
Water, Glyceryl Monostearate, Laureth-9, Mentha Piperita
Extract, Octyldodecanol, Panthenol, Paraffinum Liquidum,
Phenoxyethanol, Undecylenic Acid, Urea, Xanthan Gum, Zinc
Oxide

DESCRIPTION

Seborrheic Dermatitis is a chronic inflammatory skin condition that can fluctuate over time.

The main goal of treatment is to manage symptoms

PSODEX Seborrheic Dermatitis Therapy Cream offers a soothing formula that helps block the recurrence of Seborrheic Dermatitis symptoms with the help of SALICYLIC ACID and PYRITHIONE ZINC

PREVENTS:
Moisture loss and skin irritation

RELIEVES:
Itching, inflammation, and roughness

CONTROLS:
Flaking, scaling, eruption, and excessive sebum secretion

HELPS BLOCK:
Recurrence of Seborrheic Dermatitis symptoms

INFORMATION FOR OWNERS/CAREGIVERS

DISTRIBUTED BY: Psodex USA Inc.

9898 Bissonnet St Ste 625 Houston, TX 77036

1-844 4PSODEX www.psodexusa.com

MANUFACTURED FOR

Yesim Derma Laboratories

Active ingredient

Pyrithone Zinc 1%

Salicylic Acid 1,5%

Active ingredient

Pyrithone Zinc 1%

Salicylic Acid 1,5%

Use

For the treatment of Seborrheic Dermatitis
Provides relief from the symptoms of Seborrheic Dermatitis, including itching, redness, and scaling of the skin.

Directions

Cleanse the skin thoroughly before applying the product
Apply to affected areas with a thin layer, one to three times daily or as directed by a doctor

Ask a doctor before use if

Condition covers a large area of the body

Stop use and ask a doctor if

Condition worsens or does not improve after regular use of this product as directed.

Keep out of reach of children

If swallowed, get medical help or contact a Poison Control Center right away.

Do not use

On large or deep wounds
On damaged or irritated skin not caused by Seborrheic Dermatitis

When using this product

Avoid contact with eyes. If contact occurs, rinse eyes thoroughly with water.

Other information

Store at controlled room temperature 59-86°F

Questions or Comments

1 844 4PSODEX | info@psodexusa.com

Warnings

For external use only

Purpose

Seborrheic Dermatitis Treatment